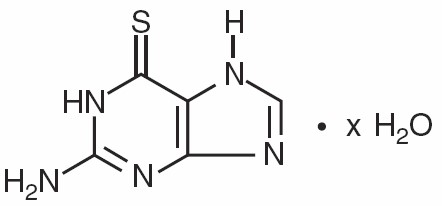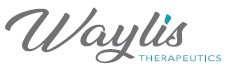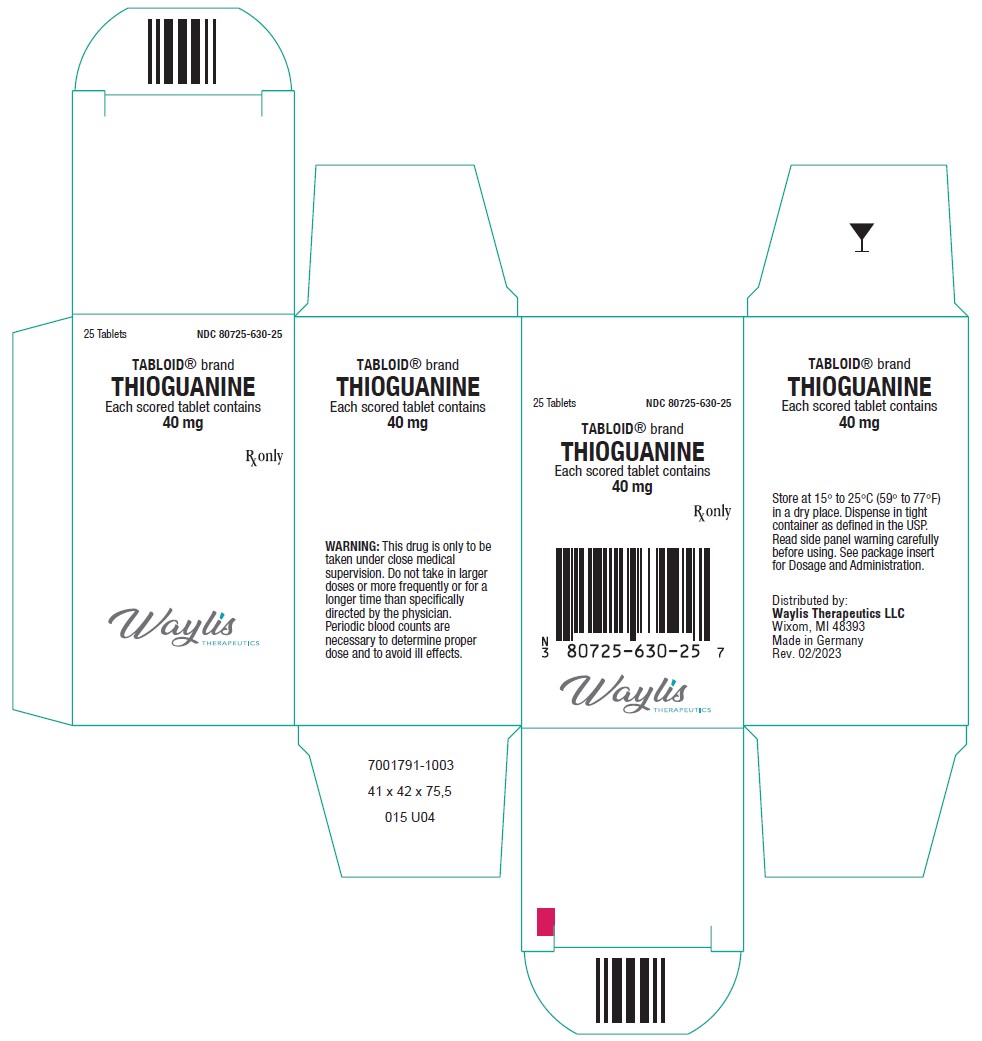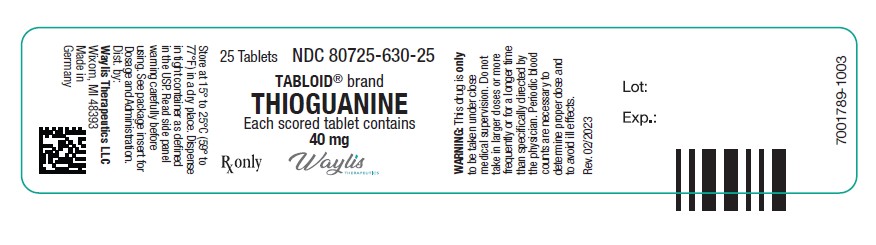 DRUG LABEL: TABLOID
NDC: 80725-630 | Form: TABLET
Manufacturer: Waylis Therapeutics LLC
Category: prescription | Type: HUMAN PRESCRIPTION DRUG LABEL
Date: 20250108

ACTIVE INGREDIENTS: THIOGUANINE 40 mg/1 1
INACTIVE INGREDIENTS: ACACIA; LACTOSE MONOHYDRATE; MAGNESIUM STEARATE; STARCH, POTATO; STEARIC ACID

TABLOID®
brand Thioguanine
40-mg Scored Tablets

CAUTION

TABLOID brand Thioguanine is a potent drug. It should not be used unless a diagnosis of acute nonlymphocytic leukemia has been adequately established and the responsible physician is knowledgeable in assessing response to chemotherapy.

DESCRIPTION

TABLOID brand Thioguanine was synthesized and developed by Hitchings, Elion, and associates at the Wellcome Research Laboratories. It is one of a large series of purine analogues which interfere with nucleic acid biosynthesis and has been found active against selected human neoplastic diseases.

Thioguanine, known chemically as 2-amino-1,7-dihydro-6H-purine-6-thione, is an analogue of the nucleic acid constituent guanine, and is closely related structurally and functionally to PURINETHOL® (mercaptopurine). Its structural formula is:

TABLOID brand Thioguanine is available in tablets for oral administration. Each scored tablet contains 40 mg thioguanine and the inactive ingredients acacia, lactose monohydrate, magnesium stearate, potato starch, and stearic acid.

CLINICAL PHARMACOLOGY

Clinical studies have shown that the absorption of an oral dose of thioguanine in humans is incomplete and variable, averaging approximately 30% of the administered dose (range: 14% to 46%). Following oral administration of ^35S-6-thioguanine, total plasma radioactivity reached a maximum at 8 hours and declined slowly thereafter. Parent drug represented only a very small fraction of the total plasma radioactivity at any time, being virtually undetectable throughout the period of measurements.

The oral administration of radiolabeled thioguanine revealed only trace quantities of parent drug in the urine. However, a methylated metabolite, 2-amino-6-methylthiopurine (MTG), appeared very early, rose to a maximum 6 to 8 hours after drug administration, and was still being excreted after 12 to 22 hours.

Radiolabeled sulfate appeared somewhat later than MTG but was the principal metabolite after 8 hours. Thiouric acid and some unidentified products were found in the urine in small amounts. Intravenous administration of ^35S-6-thioguanine disclosed a median plasma half-disappearance time of 80 minutes (range: 25 to 240 minutes) when the compound was given in single doses of 65 to 300 mg/m^2. Although initial plasma levels of thioguanine did correlate with the dose level, there was no correlation between the plasma half-disappearance time and the dose.

Thioguanine is incorporated into the DNA and the RNA of human bone marrow cells. Studies with intravenous ^35S-6-thioguanine have shown that the amount of thioguanine incorporated into nucleic acids is more than 100 times higher after 5 daily doses than after a single dose. With the 5-dose schedule, from one-half to virtually all of the guanine in the residual DNA was replaced by thioguanine. Tissue distribution studies of ^35S-6-thioguanine in mice showed only traces of radioactivity in brain after oral administration. No measurements have been made of thioguanine concentrations in human cerebrospinal fluid (CSF), but observations on tissue distribution in animals, together with the lack of CNS penetration by the closely related compound, mercaptopurine, suggest that thioguanine does not reach therapeutic concentrations in the CSF.

Monitoring of plasma levels of thioguanine during therapy is of questionable value. There is technical difficulty in determining plasma concentrations, which are seldom greater than 1 to 2 mcg/mL after a therapeutic oral dose. More significantly, thioguanine enters rapidly into the anabolic and catabolic pathways for purines, and the active intracellular metabolites have appreciably longer half-lives than the parent drug. The biochemical effects of a single dose of thioguanine are evident long after the parent drug has disappeared from plasma. Because of this rapid metabolism of thioguanine to active intracellular derivatives, hemodialysis would not be expected to appreciably reduce toxicity of the drug.

Thioguanine competes with hypoxanthine and guanine for the enzyme hypoxanthine-guanine phosphoribosyltransferase (HGPRTase) and is itself converted to 6-thioguanylic acid (TGMP). This nucleotide reaches high intracellular concentrations at therapeutic doses. TGMP interferes at several points with the synthesis of guanine nucleotides. It inhibits de novo purine biosynthesis by pseudo-feedback inhibition of glutamine-5-phosphoribosylpyrophosphate amidotransferase—the first enzyme unique to the de novo pathway for purine ribonucleotide synthesis. TGMP also inhibits the conversion of inosinic acid (IMP) to xanthylic acid (XMP) by competition for the enzyme IMP dehydrogenase. At one time TGMP was felt to be a significant inhibitor of ATP:GMP phosphotransferase (guanylate kinase), but recent results have shown this not to be so.

Thioguanylic acid is further converted to the di- and tri-phosphates, thioguanosine diphosphate (TGDP) and thioguanosine triphosphate (TGTP) (as well as their 2′-deoxyribosyl analogues) by the same enzymes which metabolize guanine nucleotides. Thioguanine nucleotides are incorporated into both the RNA and the DNA by phosphodiester linkages and it has been argued that incorporation of such fraudulent bases contributes to the cytotoxicity of thioguanine.

Thus, thioguanine has multiple metabolic effects and at present it is not possible to designate one major site of action. Its tumor inhibitory properties may be due to one or more of its effects on (a) feedback inhibition of de novo purine synthesis; (b) inhibition of purine nucleotide interconversions; or (c) incorporation into the DNA and the RNA. The net consequence of its actions is a sequential blockade of the synthesis and utilization of the purine nucleotides.

The catabolism of thioguanine and its metabolites is complex and shows significant differences between humans and the mouse. In both humans and mice, after oral administration of ^35S-6-thioguanine, urine contains virtually no detectable intact thioguanine. While deamination and subsequent oxidation to thiouric acid occurs only to a small extent in humans, it is the main pathway in mice. The product of deamination by guanase, 6-thioxanthine is inactive, having negligible antitumor activity. This pathway of thioguanine inactivation is not dependent on the action of xanthine oxidase, and an inhibitor of that enzyme (such as allopurinol) will not block the detoxification of thioguanine even though the inactive 6-thioxanthine is normally further oxidized by xanthine oxidase to thiouric acid before it is eliminated. In humans, methylation of thioguanine is much more extensive than in the mouse. The product of methylation, 2-amino-6-methylthiopurine, is also substantially less active and less toxic than thioguanine and its formation is likewise unaffected by the presence of allopurinol. Appreciable amounts of inorganic sulfate are also found in both murine and human urine, presumably arising from further metabolism of the methylated derivatives.

In some animal tumors, resistance to the effect of thioguanine correlates with the loss of HGPRTase activity and the resulting inability to convert thioguanine to thioguanylic acid. However, other resistance mechanisms, such as increased catabolism of TGMP by a nonspecific phosphatase, may be operative. Although not invariable, it is usual to find cross-resistance between thioguanine and its close analogue, PURINETHOL (mercaptopurine).

Metabolism and Genetic Polymorphism
Several published studies indicate that patients with reduced TPMT or NUDT15 activity receiving usual doses of mercaptopurine, accumulate excessive cellular concentrations of active 6-TGNs, and are at higher risk for severe myelosuppression.In a study of 1028 children with ALL, the approximate tolerated mercaptopurine dosage range for patients with TPMT and/or NUDT15 deficiency on mercaptopurine maintenance therapy (as a percentage of the planned dosage) was as follows: heterozygous for either TPMT or NUDT15, 50-90%; heterozygous for both TPMT and NUDT15, 30-50%; homozygous for either TPMT or NUDT15, 5-10%.

Approximately 0.3% (1:300) of patients of European or African ancestry have two loss-of-function alleles of the TPMT gene and have little or no TPMT activity (homozygous deficient or poor metabolizers), and approximately 10% of patients have one loss-of-function TPMT allele leading to intermediate TPMT activity (heterozygous deficient or intermediate metabolizers). The TPMT*2, TPMT*3A, and TPMT*3C alleles account for about 95% of individuals with reduced levels of TPMT activity. NUDT15 deficiency is detected in <1% of patients of European or African ancestry. Among patients of East Asian ancestry (i.e., Chinese, Japanese, Vietnamese), 2% have two loss-of-function alleles of the NUDT15 gene, and approximately 21% have one loss-of-function allele. The p.R139C variant of NUDT15 (present on the *2 and *3 alleles) is the most commonly observed, but other less common loss-of-function NUDT15 alleles have been observed.

Consider all clinical information when interpreting results from phenotypic testing used to determine the level of thiopurine nucleotides or TPMT activity in erythrocytes, since some coadministered drugs can influence measurement of TPMT activity in blood, and blood from recent transfusions will misrepresent a patient’s actual TPMT activity.

INDICATIONS AND USAGE

a) Acute Nonlymphocytic Leukemias

TABLOID brand Thioguanine is indicated for remission induction and remission consolidation treatment of acute nonlymphocytic leukemias. However, it is not recommended for use during maintenance therapy or similar long-term continuous treatments due to the high risk of liver toxicity (see WARNINGS and ADVERSE REACTIONS).

The response to this agent depends upon the age of the patient (younger patients faring better than older) and whether thioguanine is used in previously treated or previously untreated patients. Reliance upon thioguanine alone is seldom justified for initial remission induction of acute nonlymphocytic leukemias because combination chemotherapy including thioguanine results in more frequent remission induction and longer duration of remission than thioguanine alone.

b) Other Neoplasms

TABLOID brand Thioguanine is not effective in chronic lymphocytic leukemia, Hodgkin’s lymphoma, multiple myeloma, or solid tumors. Although thioguanine is one of several agents with activity in the treatment of the chronic phase of chronic myelogenous leukemia, more objective responses are observed with MYLERAN® (busulfan), and therefore busulfan is usually regarded as the preferred drug.

CONTRAINDICATIONS

Thioguanine should not be used in patients whose disease has demonstrated prior resistance to this drug. In animals and humans, there is usually complete cross-resistance between PURINETHOL (mercaptopurine) and TABLOID brand Thioguanine.

WARNINGS

SINCE DRUGS USED IN CANCER CHEMOTHERAPY ARE POTENTIALLY HAZARDOUS, IT IS RECOMMENDED THAT ONLY PHYSICIANS EXPERIENCED WITH THE RISKS OF THIOGUANINE AND KNOWLEDGEABLE IN THE NATURAL HISTORY OF ACUTE NONLYMPHOCYTIC LEUKEMIAS ADMINISTER THIS DRUG.

THIOGUANINE IS NOT RECOMMENDED FOR MAINTENANCE THERAPY OR SIMILAR LONG-TERM CONTINUOUS TREATMENTS DUE TO THE HIGH RISK OF LIVER TOXICITY ASSOCIATED WITH VASCULAR ENDOTHELIAL DAMAGE (see DOSAGE AND ADMINISTRATION and ADVERSE REACTIONS). This liver toxicity has been observed in a high proportion of children receiving thioguanine as part of maintenance therapy for acute lymphoblastic leukemia and in other conditions associated with continuous use of thioguanine. This liver toxicity is particularly prevalent in males. Liver toxicity usually presents as the clinical syndrome of hepatic veno-occlusive disease (hyperbilirubinemia, tender hepatomegaly, weight gain due to fluid retention, and ascites) or with signs of portal hypertension (splenomegaly, thrombocytopenia, and oesophageal varices). Histopathological features associated with this toxicity include hepatoportal sclerosis, nodular regenerative hyperplasia, peliosis hepatitis, and periportal fibrosis.

Thioguanine therapy should be discontinued in patients with evidence of liver toxicity as reversal of signs and symptoms of liver toxicity have been reported upon withdrawal.

Patients must be carefully monitored (see PRECAUTIONS, Laboratory Tests). Early indications of liver toxicity are signs associated with portal hypertension such as thrombocytopenia out of proportion with neutropenia and splenomegaly. Elevations of liver enzymes have also been reported in association with liver toxicity but do not always occur.

The most consistent, dose-related toxicity is bone marrow suppression. This may be manifested by anemia, leukopenia, thrombocytopenia, or any combination of these. Any one of these findings may also reflect progression of the underlying disease. Since thioguanine may have a delayed effect, it is important to withdraw the medication temporarily at the first sign of an abnormally large fall in any of the formed elements of the blood.

There are individuals with an inherited deficiency of the enzyme thiopurine methyltransferase (TPMT) who may be unusually sensitive to the myelosuppressive effects of thioguanine and prone to developing rapid bone marrow suppression following the initiation of treatment. Substantial dosage reductions may be required to avoid the development of life-threatening bone marrow suppression in these patients.

Prescribers should be aware that some laboratories offer testing for TPMT deficiency. Since bone marrow suppression may be associated with factors other than TPMT deficiency, TPMT testing may not identify all patients at risk for severe toxicity. Therefore, close monitoring of clinical and hematologic parameters is important. Bone marrow suppression could be exacerbated by coadministration with drugs that inhibit TPMT, such as olsalazine, mesalazine, or sulphasalazine.

It is recommended that evaluation of the hemoglobin concentration or hematocrit, total white blood cell count and differential count, and quantitative platelet count be obtained frequently while the patient is on thioguanine therapy. In cases where the cause of fluctuations in the formed elements in the peripheral blood is obscure, bone marrow examination may be useful for the evaluation of marrow status. The decision to increase, decrease, continue, or discontinue a given dosage of thioguanine must be based not only on the absolute hematologic values, but also upon the rapidity with which changes are occurring. In many instances, particularly during the induction phase of acute leukemia, complete blood counts will need to be done more frequently in order to evaluate the effect of the therapy. The dosage of thioguanine may need to be reduced when this agent is combined with other drugs whose primary toxicity is myelosuppression.

Myelosuppression is often unavoidable during the induction phase of adult acute nonlymphocytic leukemias if remission induction is to be successful. Whether or not this demands modification or cessation of dosage depends both upon the response of the underlying disease and a careful consideration of supportive facilities (granulocyte and platelet transfusions) which may be available. Life-threatening infections and bleeding have been observed as consequences of thioguanine-induced granulocytopenia and thrombocytopenia.

The effect of thioguanine on the immunocompetence of patients is unknown.

Pregnancy

Drugs such as thioguanine are potential mutagens and teratogens. Thioguanine may cause fetal harm when administered to a pregnant woman. Thioguanine has been shown to be teratogenic in rats when given in doses 5 times the human dose. When given to the rat on the 4th and 5th days of gestation, 13% of surviving placentas did not contain fetuses, and 19% of offspring were malformed or stunted. The malformations noted included generalized edema, cranial defects, and general skeletal hypoplasia, hydrocephalus, ventral hernia, situs inversus, and incomplete development of the limbs. There are no adequate and well-controlled studies in pregnant women. If this drug is used during pregnancy, or if the patient becomes pregnant while taking the drug, the patient should be apprised of the potential hazard to the fetus. Women of childbearing potential should be advised to avoid becoming pregnant.

PRECAUTIONS

General

Although the primary toxicity of thioguanine is myelosuppression, other toxicities have occasionally been observed, particularly when thioguanine is used in combination with other cancer chemotherapeutic agents.

A few cases of jaundice have been reported in patients with leukemia receiving thioguanine. Among these were 2 adult male patients and 4 pediatric patients with acute myelogenous leukemia and an adult male with acute lymphocytic leukemia who developed hepatic veno-occlusive disease while receiving chemotherapy for their leukemia. Six patients had received cytarabine prior to treatment with thioguanine, and some were receiving other chemotherapy in addition to thioguanine when they became symptomatic. While hepatic veno-occlusive disease has not been reported in patients treated with thioguanine alone, it is recommended that thioguanine be withheld if there is evidence of toxic hepatitis or biliary stasis, and that appropriate clinical and laboratory investigations be initiated to establish the etiology of the hepatic dysfunction. Deterioration in liver function studies during thioguanine therapy should prompt discontinuation of treatment and a search for an explanation of the hepatotoxicity.

Administration of live vaccines to immunocompromised patients should be avoided.

Information for Patients

Patients should be informed that the major toxicities of thioguanine are related to myelosuppression, hepatotoxicity, and gastrointestinal toxicity. Patients should never be allowed to take the drug without medical supervision and should be advised to consult their physician if they experience fever, sore throat, jaundice, nausea, vomiting, signs of local infection, bleeding from any site, or symptoms suggestive of anemia. Women of childbearing potential should be advised to avoid becoming pregnant.

Laboratory Tests

Prescribers should be aware that some laboratories offer testing for TPMT deficiency (see WARNINGS).

It is advisable to monitor liver function tests (serum transaminases, alkaline phosphatase, bilirubin) at weekly intervals when first beginning therapy and at monthly intervals thereafter. It may be advisable to perform liver function tests more frequently in patients with known pre-existing liver disease or in patients who are receiving thioguanine and other hepatotoxic drugs. Patients should be instructed to discontinue thioguanine immediately if clinical jaundice is detected (see WARNINGS).

Drug Interactions

There is usually complete cross-resistance between PURINETHOL (mercaptopurine) and TABLOID brand Thioguanine.

As there is in vitro evidence that aminosalicylate derivatives (e.g., olsalazine, mesalazine, or sulphasalazine) inhibit the TPMT enzyme, they should be administered with caution to patients receiving concurrent thioguanine therapy (see WARNINGS).

Carcinogenesis, Mutagenesis, Impairment of Fertility

In view of its action on cellular DNA, thioguanine is potentially mutagenic and carcinogenic, and consideration should be given to the theoretical risk of carcinogenesis when thioguanine is administered (see WARNINGS).

Lactation

It is not known whether this drug is excreted in human milk. Because of the potential for tumorigenicity shown for thioguanine, a decision should be made whether to discontinue nursing or to discontinue the drug, taking into account the importance of the drug to the mother.

Pediatric Use

See DOSAGE AND ADMINISTRATION section.

Geriatric Use

Clinical studies of thioguanine did not include sufficient numbers of subjects aged 65 and over to determine whether they respond differently from younger subjects. Other reported clinical experience has not identified differences in responses between the elderly and younger patients. In general, dose selection for an elderly patient should be cautious, usually starting at the low end of the dosing range, reflecting the greater frequency of decreased hepatic, renal, or cardiac function, and of concomitant disease or other drug therapy.

ADVERSE REACTIONS

To report SUSPECTED ADVERSE REACTIONS, contact Waylis Therapeutics LLC Toll-Free at 1-888-514-4727 or FDA at 1-800-FDA-1088 or www.fda.gov/medwatch.
The most frequent adverse reaction to thioguanine is myelosuppression. The induction of complete remission of acute myelogenous leukemia usually requires combination chemotherapy in dosages which produce marrow hypoplasia. Since consolidation and maintenance of remission are also effected by multiple-drug regimens whose component agents cause myelosuppression, pancytopenia is observed in nearly all patients. Dosages and schedules must be adjusted to prevent life-threatening cytopenias whenever these adverse reactions are observed.

Hyperuricemia frequently occurs in patients receiving thioguanine as a consequence of rapid cell lysis accompanying the antineoplastic effect. Adverse effects can be minimized by increased hydration, urine alkalinization, and the prophylactic administration of a xanthine oxidase inhibitor such as ZYLOPRIM® (allopurinol). Unlike PURINETHOL (mercaptopurine) and IMURAN® (azathioprine), thioguanine may be continued in the usual dosage when allopurinol is used conjointly to inhibit uric acid formation. Less frequent adverse reactions include nausea, vomiting, anorexia, and stomatitis. Intestinal necrosis and perforation have been reported in patients who received multiple-drug chemotherapy including thioguanine.

Hepatic Effects

Liver toxicity associated with vascular endothelial damage has been reported when thioguanine is used in maintenance or similar long-term continuous therapy which is not recommended (see WARNINGS and DOSAGE AND ADMINISTRATION). This usually presents as the clinical syndrome of hepatic veno-occlusive disease (hyperbilirubinemia, tender hepatomegaly, weight gain due to fluid retention, and ascites) or signs and symptoms of portal hypertension (splenomegaly, thrombocytopenia, and esophageal varices). Elevation of liver transaminases, alkaline phosphatase, and gamma glutamyl transferase and jaundice may also occur. Histopathological features associated with this toxicity include hepatoportal sclerosis, nodular regenerative hyperplasia, peliosis hepatitis, and periportal fibrosis.

Liver toxicity during short-term cyclical therapy presents as veno-occlusive disease. Reversal of signs and symptoms of this liver toxicity has been reported upon withdrawal of short-term or long-term continuous therapy.

Centrilobular hepatic necrosis has been reported in a few cases; however, the reports are confounded by the use of high doses of thioguanine, other chemotherapeutic agents, and oral contraceptives and chronic alcohol abuse.

OVERDOSAGE

Signs and symptoms of overdosage may be immediate, such as nausea, vomiting, malaise, hypotension, and diaphoresis; or delayed, such as myelosuppression and azotemia. It is not known whether thioguanine is dialyzable. Hemodialysis is thought to be of marginal use due to the rapid intracellular incorporation of thioguanine into active metabolites with long persistence. The oral LD50 of thioguanine was determined to be 823 mg/kg ± 50.73 mg/kg and 740 mg/kg ± 45.24 mg/kg for male and female rats, respectively. Symptoms of overdosage may occur after a single dose of as little as 2.0 to 3.0 mg/kg thioguanine. As much as 35 mg/kg has been given in a single oral dose with reversible myelosuppression observed. There is no known pharmacologic antagonist of thioguanine. The drug should be discontinued immediately if unintended toxicity occurs during treatment. Severe hematologic toxicity may require supportive therapy with platelet transfusions for bleeding, and granulocyte transfusions and antibiotics if sepsis is documented. If a patient is seen immediately following an accidental overdosage of the drug, it may be useful to induce emesis.

DOSAGE AND ADMINISTRATION

TABLOID brand Thioguanine is administered orally. The dosage which will be tolerated and effective varies according to the stage and type of neoplastic process being treated. Because the usual therapies for adult and pediatric acute nonlymphocytic leukemias involve the use of thioguanine with other agents in combination, physicians responsible for administering these therapies should be experienced in the use of cancer chemotherapy and in the chosen protocol.

Patients with homozygous deficiency of either TPMT or NUDT15 enzyme typically require 10% or less of the standard thioguanine dosage. Reduce initial dosage in patients who are known to have homozygous TPMT or NUDT15 deficiency. Most of the patients with heterozygous TPMT or NUDT15 deficiency tolerate recommended thioguanine doses, but some require dose reduction based on toxicities. Patients who are heterozygous for both TPMT and NUDT15 may require more substantial dosage reduction. Reduce the dosage based on tolerability.

Ninety-six (59%) of 163 pediatric patients with previously untreated acute nonlymphocytic leukemia obtained complete remission with a multiple-drug protocol including thioguanine, prednisone, cytarabine, cyclophosphamide, and vincristine. Remission was maintained with daily thioguanine, 4-day pulses of cytarabine and cyclophosphamide, and a single dose of vincristine every 28 days. The median duration of remission was 11.5 months.

Fifty-three percent of previously untreated adults with acute nonlymphocytic leukemias attained remission following use of the combination of thioguanine and cytarabine according to a protocol developed at The Memorial Sloan-Kettering Cancer Center. A median duration of remission of 8.8 months was achieved with the multiple-drug maintenance regimen which included thioguanine.

On those occasions when single-agent chemotherapy with thioguanine may be appropriate, the usual initial dosage for pediatric patients and adults is approximately 2 mg/kg of body weight per day. If, after 4 weeks on this dosage, there is no clinical improvement and no leukocyte or platelet depression, the dosage may be cautiously increased to 3 mg/kg/day. The total daily dose may be given at one time.

The dosage of thioguanine used does not depend on whether or not the patient is receiving ZYLOPRIM (allopurinol); this is in contradistinction to the dosage reduction which is mandatory when PURINETHOL (mercaptopurine) or IMURAN (azathioprine) is given simultaneously with allopurinol.

Procedures for proper handling and disposal of anticancer drugs should be considered. Several guidelines on this subject have been published.^1-8

There is no general agreement that all of the procedures recommended in the guidelines are necessary or appropriate.

HOW SUPPLIED

A biconvex, round white to off-white tablet, one side imprinted T40 and with a scorebar and the other side plain: in bottles of 25 tablets (NDC 80725-630-25).

Store at 15° to 25°C (59° to 77°F) in a dry place.

REFERENCES

1. ONS Clinical Practice Committee. Cancer Chemotherapy Guidelines and Recommendations for Practice. Pittsburgh, PA: Oncology Nursing Society; 1999:32-41.
2. Recommendations for the safe handling of parenteral antineoplastic drugs. Washington, DC: Division of Safety, Clinical Center Pharmacy Department and Cancer Nursing Services, National Institutes of Health and Human Services, 1992, US Dept of Health and Human Services, Public Health Service publication NIH 92-2621.
3. AMA Council on Scientific Affairs. Guidelines for handling parenteral antineoplastics. JAMA. 1985;253:1590-1591.
4. National Study Commission on Cytotoxic Exposure. Recommendations for handling cytotoxic agents. 1987. Available from Louis P. Jeffrey, Chairman, National Study Commission on Cytotoxic Exposure. Massachusetts College of Pharmacy and Allied Health Sciences, 179 Longwood Avenue, Boston, MA 02115.
5. Clinical Oncological Society of Australia. Guidelines and recommendations for safe handling of antineoplastic agents. Med J Australia. 1983;1:426-428.
6. Jones RB, Frank R, Mass T. Safe handling of chemotherapeutic agents: a report from the Mount Sinai Medical Center. CA-A Cancer J for Clin. 1983;33:258-263.
7. American Society of Hospital Pharmacists. ASHP technical assistance bulletin on handling cytotoxic and hazardous drugs. Am J Hosp Pharm. 1990;47:1033-1049.
8. Controlling Occupational Exposure to Hazardous Drugs. (OSHA Work-Practice Guidelines.) Am J Health-Syst Pharm. 1996;53:1669-1685.

Distributed by: Waylis Therapeutics LLC
Wixom, MI 48393
Made in Germany
Rev. 02/2023

Principal Display Panel

NDC 80725-630-25

TABLOID® brand

THIOGUANINE

Each scored tablet contains 40 mg

Rx only

25 Tablets